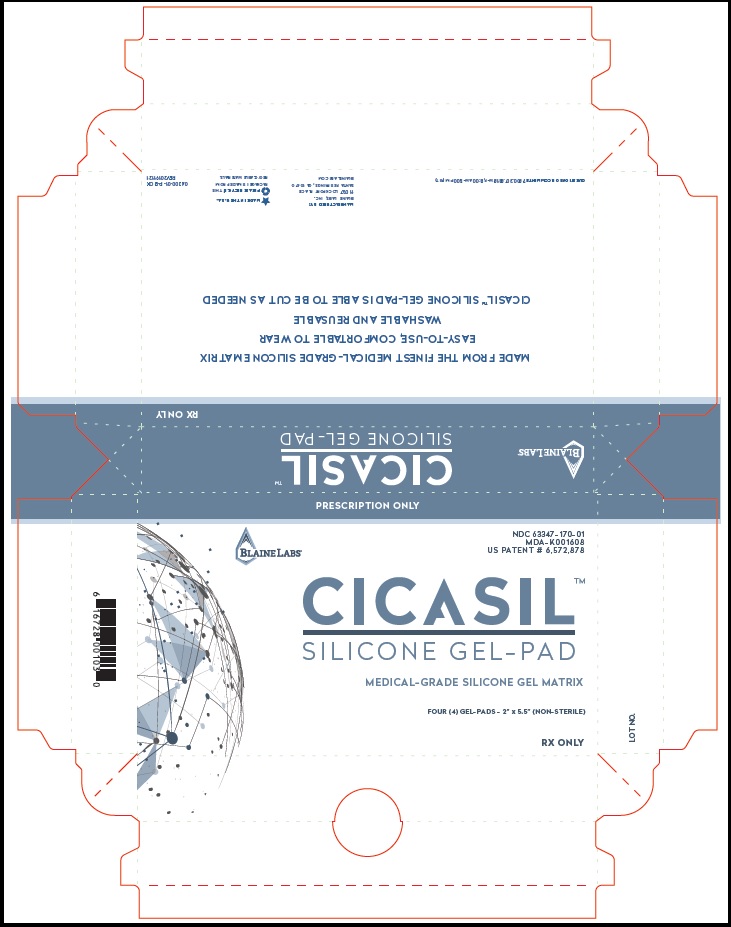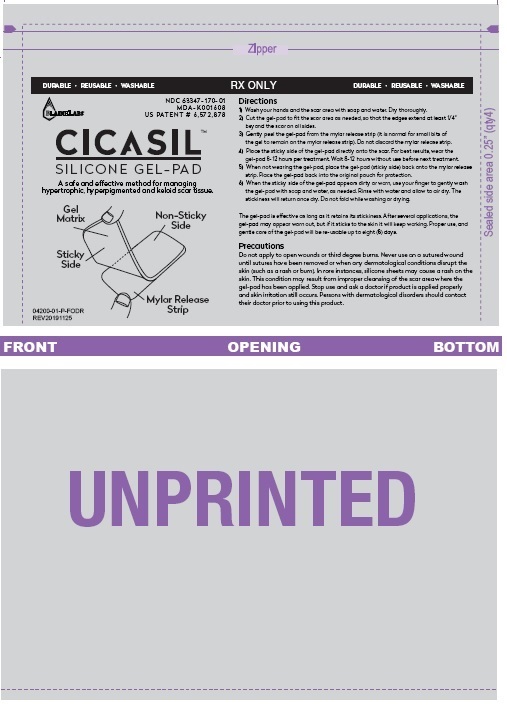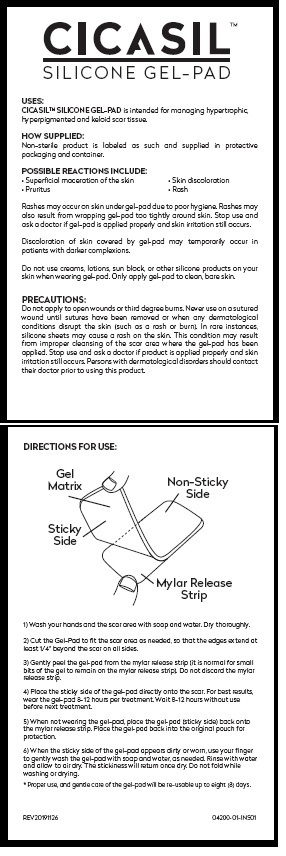 DRUG LABEL: CICASIL SILICONE GEL-PAD
NDC: 63347-170
Manufacturer: Blaine Labs Inc.
Category: other | Type: MEDICAL DEVICE
Date: 20200128

CICASILTM SILICONE GEL-PAD

PRESCRIPTION ONLY

USES:
CICASIL™ SILICONE GEL-PAD is intended for managing hypertrophic, hyperpigmented and keloid scar tissue.

HOW SUPPLIED:
Non-sterile product is labeled as such and supplied in protective packaging and container.

POSSIBLE REACTIONS INCLUDE:
• Superficial maceration of the skin • Skin discoloration
• Pruritus • Rash
Rashes may occur on skin under gel-pad due to poor hygiene. Rashes may also result from wrapping gel-pad too tightly around skin. Stop use and ask a doctor if gel-pad is applied properly and skin irritation still occurs.

Discoloration of skin covered by gel-pad may temporarily occur in patients with darker complexions.

Do not use creams, lotions, sun block, or other silicone products on your skin when wearing gel-pad. Only apply gel-pad to clean, bare skin.

PRECAUTIONS:
Do not apply to open wounds or third degree burns. Never use on a sutured wound until sutures have been removed or when any dermatological conditions disrupt the skin (such as a rash or burn). In rare instances, silicone sheets may cause a rash on the skin. This condition may result from improper cleansing of the scar area where the gel-pad has been applied. Stop use and ask a doctor if product is applied properly and skin irritation still occurs. Persons with dermatological disorders should contact their doctor prior to using this product.

DIRECTIONS FOR USE:
1) Wash your hands and the scar area with soap and water. Dry thoroughly.

2) Cut the Gel-Pad to fit the scar area as needed, so that the edges extend at
least 1/4” beyond the scar on all sides.

3) Gently peel the gel-pad from the mylar release strip (it is normal for small
bits of the gel to remain on the mylar release strip). Do not discard the mylar
release strip.

4) Place the sticky side of the gel-pad directly onto the scar. For best results,
wear the gel-pad 8-12 hours per treatment. Wait 8-12 hours without use
before next treatment.

5) When not wearing the gel-pad, place the gel-pad (sticky side) back onto
the mylar release strip. Place the gel-pad back into the original pouch for protection.

6) When the sticky side of the gel-pad appears dirty or worn, use your finger
to gently wash the gel-pad with soap and water, as needed. Rinse with water
and allow to air dry. The stickiness will return once dry. Do not fold while
washing or drying.

* Proper use, and gentle care of the gel-pad will be re-usable up to eight (8) days.

Product Package

PRESCRIPTION ONLY

BLAINE LABS

NDC 63347- 170-01
MDA-K001608
US PATENT # 6,572,878

CICASILTM
S I L I CONE GEL-PAD

MEDICAL-GRADE SILICONE GEL MATRIX
FOUR (4) GEL-PADS - 2” x 5.5” (NON-STERILE)

RX ONLY

BLAINE LABS

CICASILTM
S I L I CONE GEL-PAD

RX ONLY

MADE FROM THE FINEST MEDICAL-GRADE SILICONE MATRIX
EASY-TO-USE, COMFORTABLE TO WEAR
WASHABLE AND REUSABLE
CICASIL™ SILICONE GEL-PAD IS ABLE TO BE CUT AS NEEDED

QUESTIONS OR COMMENTS? 800.307.8818 M-F, 8:00 AM-5:00 PM (PST)

MANUFACTURED BY:
BLAINE LABS, INC.
1 1 0 3 7 LOCKPORT PLACE
SANTA FE SPRINGS, CA 90670
BLAINELABS.COM

PLEASE RECYCLE! THIS
PACKAGE IS MADE FROM
RECYCLABLE MATERIALS.

04200-01-P-BOX

REV20191121

LOT NO

res